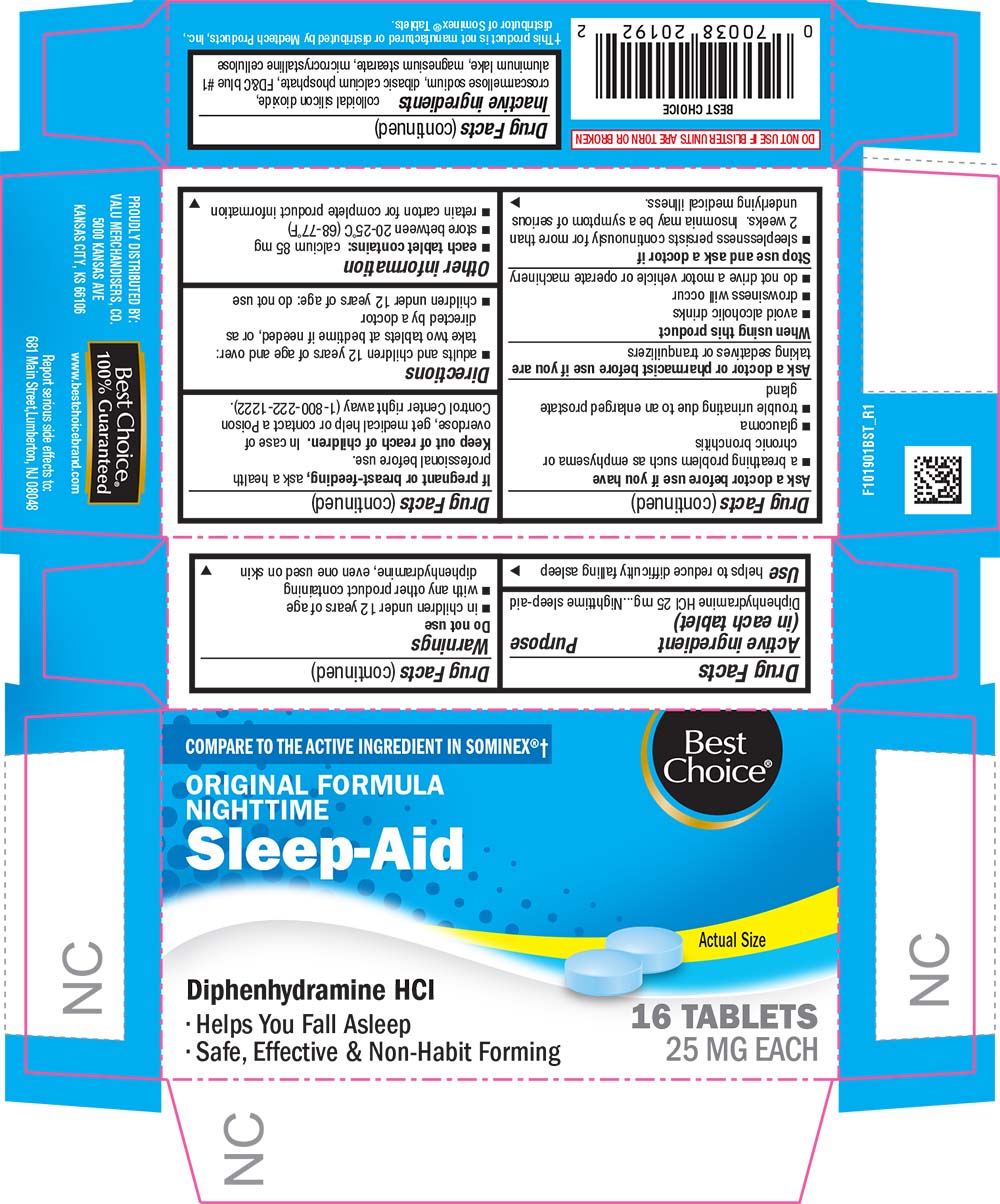 DRUG LABEL: Nighttime Sleep Aid
NDC: 63941-219 | Form: TABLET
Manufacturer: VALU MERCHANDISERS COMPANY
Category: otc | Type: HUMAN OTC DRUG LABEL
Date: 20251211

ACTIVE INGREDIENTS: DIPHENHYDRAMINE HYDROCHLORIDE 25 mg/1 1
INACTIVE INGREDIENTS: SILICON DIOXIDE; CROSCARMELLOSE SODIUM; CALCIUM PHOSPHATE, DIBASIC, ANHYDROUS; FD&C BLUE NO. 1; ALUMINUM OXIDE; MAGNESIUM STEARATE; CELLULOSE, MICROCRYSTALLINE

1019-BST-2021-1116

Drug Facts

Active ingredient (in each tablet)

Diphenhydramine HCl 25 mg

Purpose

Nighttime sleep-aid

Use

helps to reduce difficulty falling asleep

Warnings

Do not use

- in children under 12 years of age
- with any other product containing diphenhydramine, even one used on skin

Ask a doctor before use if you have

- a breathing problem such as emphysema or chronic bronchitis
- glaucoma
- trouble urinating due to an enlarged prostate gland

Ask a doctor or pharmacist before use if you are taking sedatives or tranquilizers

When using this product

- avoid alcoholic drinks
- drowsiness will occur
- do not drive a motor vehicle or operate machinery

Stop use and ask a doctor if

- sleeplessness persists continuously for more than 2 weeks.

Insomnia may be a symptom of serious underlying medical illness.

PREGNANCY OR BREAST FEEDING

If pregnant or breast-feeding, ask a health professional before use.

Keep out of reach of children.

In case of overdose, get medical help or contact a Poison Control Center right away (1-800-222-1222).

Directions

- adults and children 12 years of age and over: take two tablets at bedtime if needed, or as directed by a doctor
- children under 12 years of age: do not use

Other information

- each tablet contains: calcium 85 mg
- store between 20-25°C (68-77°F)
- retain carton for complete product information

Inactive ingredients

colloidal silicon dioxide, croscarmellose sodium, dibasic calcium phosphate, FD&C blue #1 aluminum lake, magnesium stearate, microcrystalline cellulose

PRINCIPAL DISPLAY PANEL

COMPARE TO THE ACTIVE INGREDIENT IN SOMINEX®†

Best Choice®

ORIGINAL FORMULA

NIGHTTIME

Sleep-Aid

Actual Size

Diphenhydramine HCl

• Helps You Fall Asleep

• Safe, Effective & Non-Habit Forming

16 TABLETS

25 MG EACH